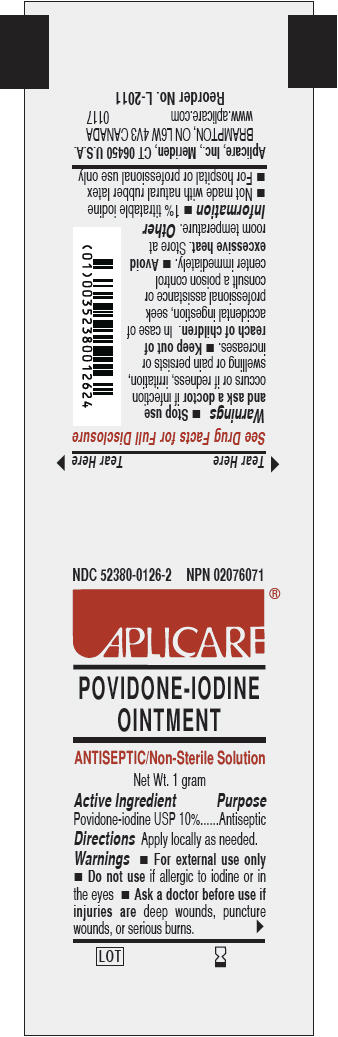 DRUG LABEL: Aplicare Povidone-Iodine
NDC: 52380-0126 | Form: OINTMENT
Manufacturer: Aplicare Products, LLC
Category: otc | Type: HUMAN OTC DRUG LABEL
Date: 20230216

ACTIVE INGREDIENTS: POVIDONE-IODINE 10 mg/1 g
INACTIVE INGREDIENTS: GLYCERIN; PROPYLENE GLYCOL; POLYETHYLENE GLYCOL 1450

0126 Povidone-Iodine Ointment

Active Ingredient

Povidone-iodine USP 10%

Purpose

Antiseptic

Use

antiseptic skin preparation

Warnings

- For external use only

Do not use

- if allergic to iodine or in the eyes

Ask a doctor before use if injuries are

- deep wounds, puncture wounds, or serious burns

Stop use and ask a doctor

- if infection occurs or if redness, irritation, swelling or pain persists or increases.

Keep out of reach of children.

In case of accidental ingestion, seek professional assistance or consult a poison control center immediately.

STORAGE AND HANDLING

- Avoid excessive heat. Store at room temperature.

Directions

Apply locally as needed.

Other Information

- 1% titratable iodine
- Not made with natural rubber latex
- for hospital or professional use only

Inactive ingredients

glycerin, polyethylene glycol, propylene glycol